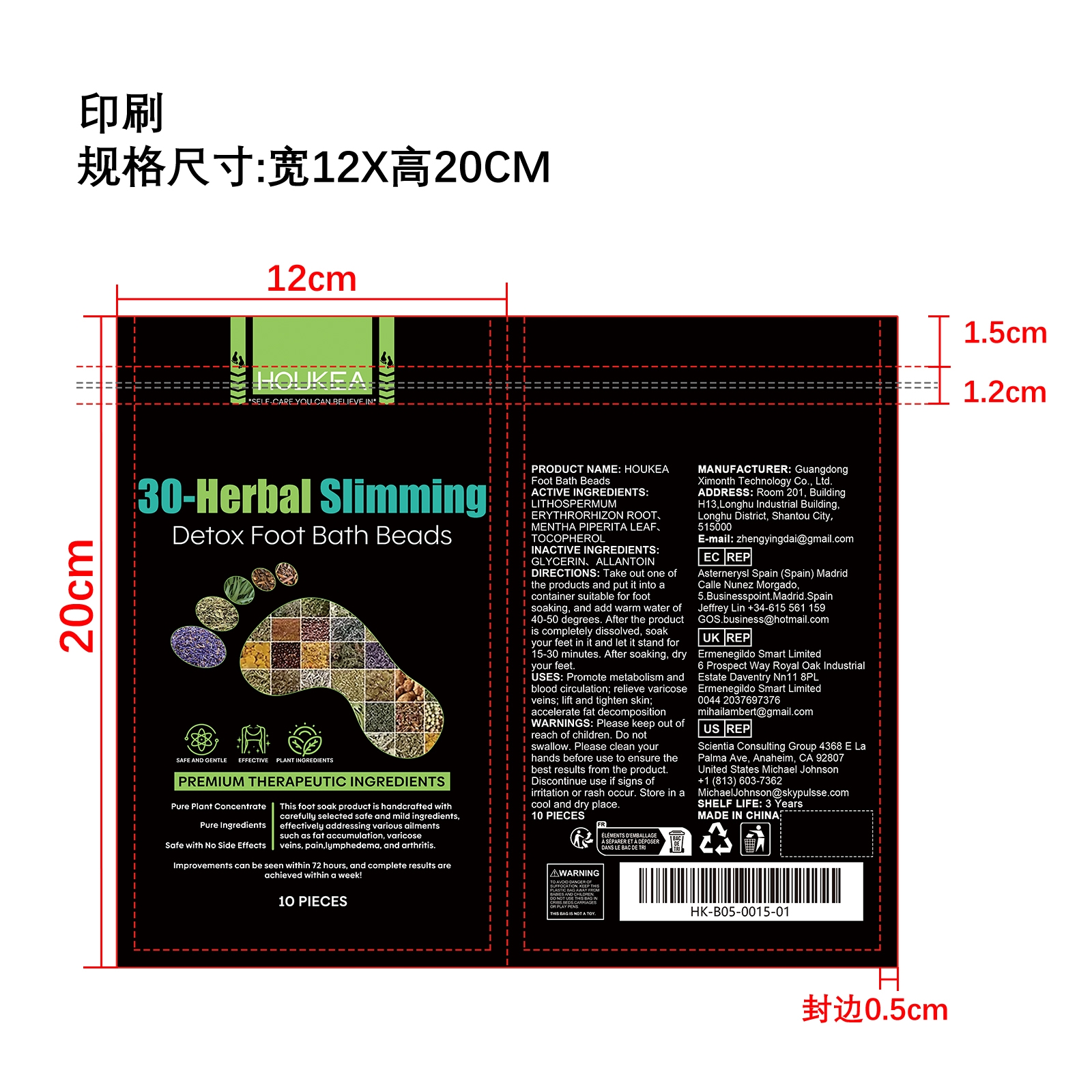 DRUG LABEL: HOUKEA Foot Bath Beads
NDC: 84660-102 | Form: LIQUID
Manufacturer: Guangdong Ximonth Technology Co., Ltd.
Category: otc | Type: HUMAN OTC DRUG LABEL
Date: 20241031

ACTIVE INGREDIENTS: TOCOPHEROL 1 mg/10 mg; LITHOSPERMUM ERYTHRORHIZON ROOT 2 mg/10 mg; MENTHA PIPERITA LEAF 1 mg/10 mg
INACTIVE INGREDIENTS: GLYCERIN 4 mg/10 mg; ALLANTOIN 2 mg/10 mg

Active Ingredient(s)

LITHOSPERMUM ERYTHRORHIZON ROOT、MENTHA PIPERITA LEAF、 TOCOPHEROL

Purpose

Promote metabolism and blood circulation; relieve varicose veins; lift and tighten skin; accelerate fat decomposition

Use

Take out one ofthe products and put it into a container suitable for foot soaking, and add warm water of 40-50 degrees. After the product is completely dissolved, soak your feet in it and let it stand for 15-30 minutes. After soaking, dry your feet.

Warnings

Please keep out of reach of children.Do not swallow.Please clean your hands before use to ensure the best results from the product.Discontinue use if signs of irritation or rash occur.Store in a cool and dry place.

Do not use

Discontinue use if signs of irritation or rash occur.

Stop Use

Discontinue use if signs of irritation or rash occur.

KEEP OUT OF REACH OF CHILDREN

Please keep out of reach of children. Do not swallow.

SAFE HANDLING WARNING

Store in a cool and dry place.

INACTIVE INGREDIENT

GLYCERIN、ALLANTOIN